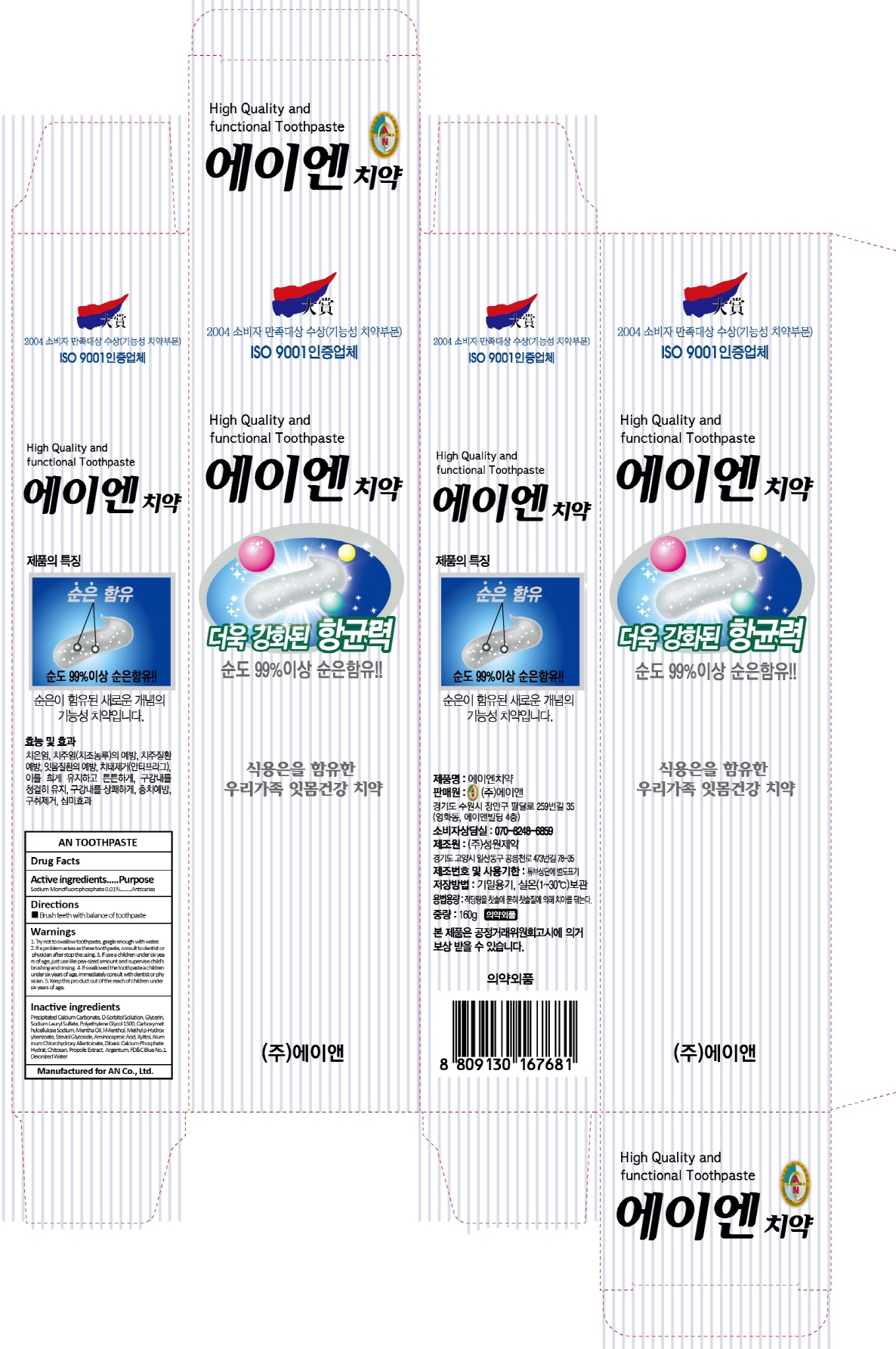 DRUG LABEL: AN TOOTH
NDC: 69153-120 | Form: PASTE, DENTIFRICE
Manufacturer: AN Co Ltd.
Category: otc | Type: HUMAN OTC DRUG LABEL
Date: 20170227

ACTIVE INGREDIENTS: SODIUM MONOFLUOROPHOSPHATE 0.016 g/160 g
INACTIVE INGREDIENTS: Glycerin; Polyethylene Glycol 1500

ACTIVE INGREDIENT

Active ingredients: Sodium Monofluorophosphate 0.01%

INACTIVE INGREDIENT

Inactive ingredients: Precipitated Calcium Carbonate, D-Sorbitol Solution, Glycerin, Sodium Lauryl Sulfate, Polyethylene Glycol 1500, Carboxymethylcellulose Sodium, Mentha Oil, l-Menthol, Methyl ρ-Hydroxybenzoate, Steviol Glycoside, Aminocaproic Acid, Xylitol, Aluminum Chlorohydroxy Allantoinate, Dibasic Calcium Phosphate Hydrat, Chitosan, Propolis Extract, Argentum, FD&C Blue No.1, Deionized Water

PURPOSE

Purpose: Anticaries

WARNINGS

Warnings: 1. Try not to swallow toothpaste, gargle enough with water. 2. If a problem arises as these toothpaste, consult to dentist or physician after stop the using. 3. If use a children under six years of age, just use like pea-sized amount and supervise child’s brushing and rinsing. 4. If swallowed the toothpaste a children under six years of age, immediately consult with dentist or physician. 5. Keep this product out of the reach of children under six years of age.

KEEP OUT OF REACH OF CHILDREN

Keep this product out of the reach of children under six years of age.

Directions

Directions: Brush teeth with balance of toothpaste.

Directions

Directions: Brush teeth with balance of toothpaste.